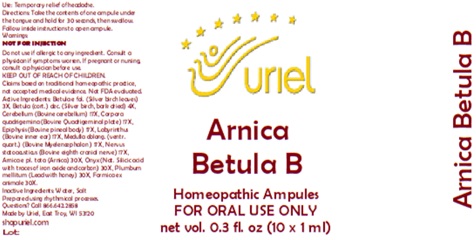 DRUG LABEL: Arnica Betula B
NDC: 48951-1384 | Form: LIQUID
Manufacturer: Uriel Pharmacy Inc.
Category: homeopathic | Type: HUMAN OTC DRUG LABEL
Date: 20260202

ACTIVE INGREDIENTS: BETULA PUBESCENS LEAF 3 [hp_X]/1 mL; BETULA PUBESCENS BARK 4 [hp_X]/1 mL; BOS TAURUS CEREBELLUM 17 [hp_X]/1 mL; BOS TAURUS BRAIN 17 [hp_X]/1 mL; BOS TAURUS PINEAL GLAND 17 [hp_X]/1 mL; SUS SCROFA EAR 17 [hp_X]/1 mL; BOS TAURUS NERVE 17 [hp_X]/1 mL; ARNICA MONTANA 30 [hp_X]/1 mL; LEAD 30 [hp_X]/1 mL; FORMICA RUFA 30 [hp_X]/1 mL; BIFENTHRIN 30 [hp_X]/1 mL; BOS TAURUS MESENCEPHALON 17 [hp_X]/1 mL; HONEY 30 [hp_X]/1 mL
INACTIVE INGREDIENTS: WATER; SODIUM CHLORIDE

Arnica Betula B

PURPOSE

Use: Temporary relief of headache.

INDICATIONS AND USAGE

FOR ORAL USE ONLY

DOSAGE AND ADMINISTRATION

Directions: Take the contents of one ampule under the tongue and hold for 30 seconds, then swallow. Follow inside instructions to open ampule.

Warnings:
NOT FOR INJECTION
Do not use if allergic to any ingredient. Consult a physician if symptoms worsen. If pregnant or nursing, consult a physician before use.
Claims based on traditional homeopathic practice, not accepted medical evidence. Not FDA evaluated.

KEEP OUT OF REACH OF CHILDREN.

ACTIVE INGREDIENT

Active Ingredients: Betula e fol. (Silver birch leaves) 3X, Betula (cort.) dec. (Silver birch, bark dried) 4X, Cerebellum (Bovine cerebellum) 17X, Corpora quadrigemina (Bovine Quadrigeminal plate) 17X, Epiphysis (Bovine pineal body) 17X, Labyrinthus (Bovine inner ear) 17X, Medulla oblong. (ventr. quart.) (Bovine Myelencephalon) 17X, Nervus statoacusticus (Bovine eighth cranial nerve) 17X, Arnica e pl. tota (Arnica) 30X, Onyx (Nat. Silicic acid with traces of iron oxide and carbon) 30X, Plumbum mellitum (Lead with honey) 30X, Formica ex animale 30X

Inactive Ingredients: Water, Salt

Prepared using rhythmical processes.

QUESTIONS

Questions? Call 866.642.2858 Made by Uriel, East Troy, WI 53120 shopuriel.com Lot: